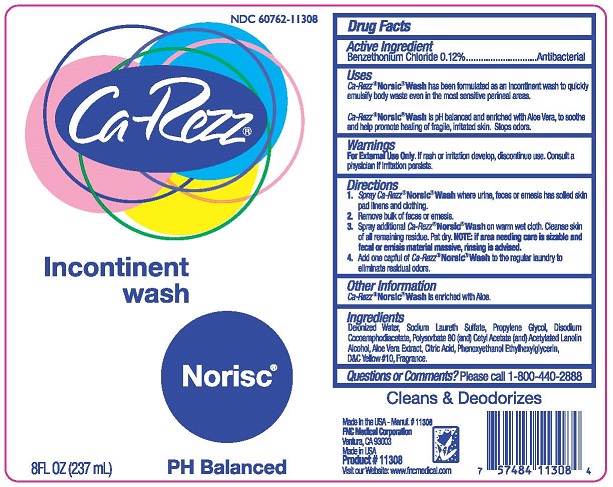 DRUG LABEL: CA-REZZ - NORISC - INCONTINENT WASH
NDC: 60762-113 | Form: SOLUTION
Manufacturer: FNC MEDICAL CORPORATION
Category: otc | Type: HUMAN OTC DRUG LABEL
Date: 20251022

ACTIVE INGREDIENTS: BENZETHONIUM CHLORIDE 0.12 g/100 mL
INACTIVE INGREDIENTS: WATER; PROPYLENE GLYCOL; DISODIUM COCOAMPHODIACETATE; POLYSORBATE 80; CETYL ACETATE; ACETYLATED LANOLIN ALCOHOLS; ALOE VERA WHOLE; ANHYDROUS CITRIC ACID; PHENOXYETHANOL; ETHYLHEXYLGLYCERIN; D&C YELLOW NO. 10; SODIUM LAURETH SULFATE

FNC - CA-REZZ - NORISC - INCONTINENT WASH 8oz (60762-113)

ACTIVE INGREDIENT

BENZETHONIUM CHLORIDE 0.12%

PURPOSE

ANTIBACTERIAL

USES

CA-REZZ NORSIC WASH HAS BEEN FORMULATED AS AN INCONTINENT WASH TO QUICKLY EMULSIFY BODY WASTE EVEN IN THE MOST SENSITIVE PERINEAL AREAS.

CA-REZZ NORSIC WASH IS PH BALANCED AND ENRICHED WITH ALOE VERA, TO SOOTHE AND HELP PROMOTE HEALING OF FRAGILE, IRRITATED SKIN. STOPS ODORS.

WARNINGS

FOR EXTERNAL USE ONLY. IF RASH OR IRRITATION DEVELOP, DISCONTINUE USE. CONSULT A PHYSICIAN IF IRRITATION PERSISTS.

KEEP OUT OF REACH OF CHILDREN.

DIRECTIONS

1. SPRAY CA-REZZ NORSIC WASH WHERE URINE, FECES OR EMESIS HAS SOILED SKIN PAD LINENS AND CLOTHING.
2. REMOVE BULK OF FECES OR EMESIS.
3. SPRAY ADDITIONAL CA-REZZ NORSIC WASH ON WARM WET CLOTH. CLEANSE SKIN OF ALL REMAINING RESIDUE. PAT DRY. NOTE: IF AREA NEEDING CARE IS SIZEABLE AND FECAL OR EMESIS MATERIAL MASSIVE, RINSING IS ADVISED.
4. ADD ONE CAPFUL OF CA-REZZ NORSIC WASH TO THE REGULAR LAUNDRY TO ELIMINATE RESIDUAL ODORS.

OTHER INFORMATION

CA-REZZ NORSIC WASH IS ENRICHED WITH ALOE.

INGREDIENTS

DEIONIZED WATER, SODIUM LAURETH SULFATE, PROPYLENE GLYCOL, DISODIUM COCOAMPHODIACETATE, POLYSORBATE 80 (AND) CETYL ALCOHOL (AND) ACETYLATED LANOLIN ALCOHOL, ALOE VERA EXTRACT, CITRIC ACID, PHENOXYETHANOL, ETHYHEXYLGLYCERIN, D&C YELLOW #10, FRAGRANCE.

QUESTIONS OR COMMENTS?

PLEASE CALL 1-800-440-2888